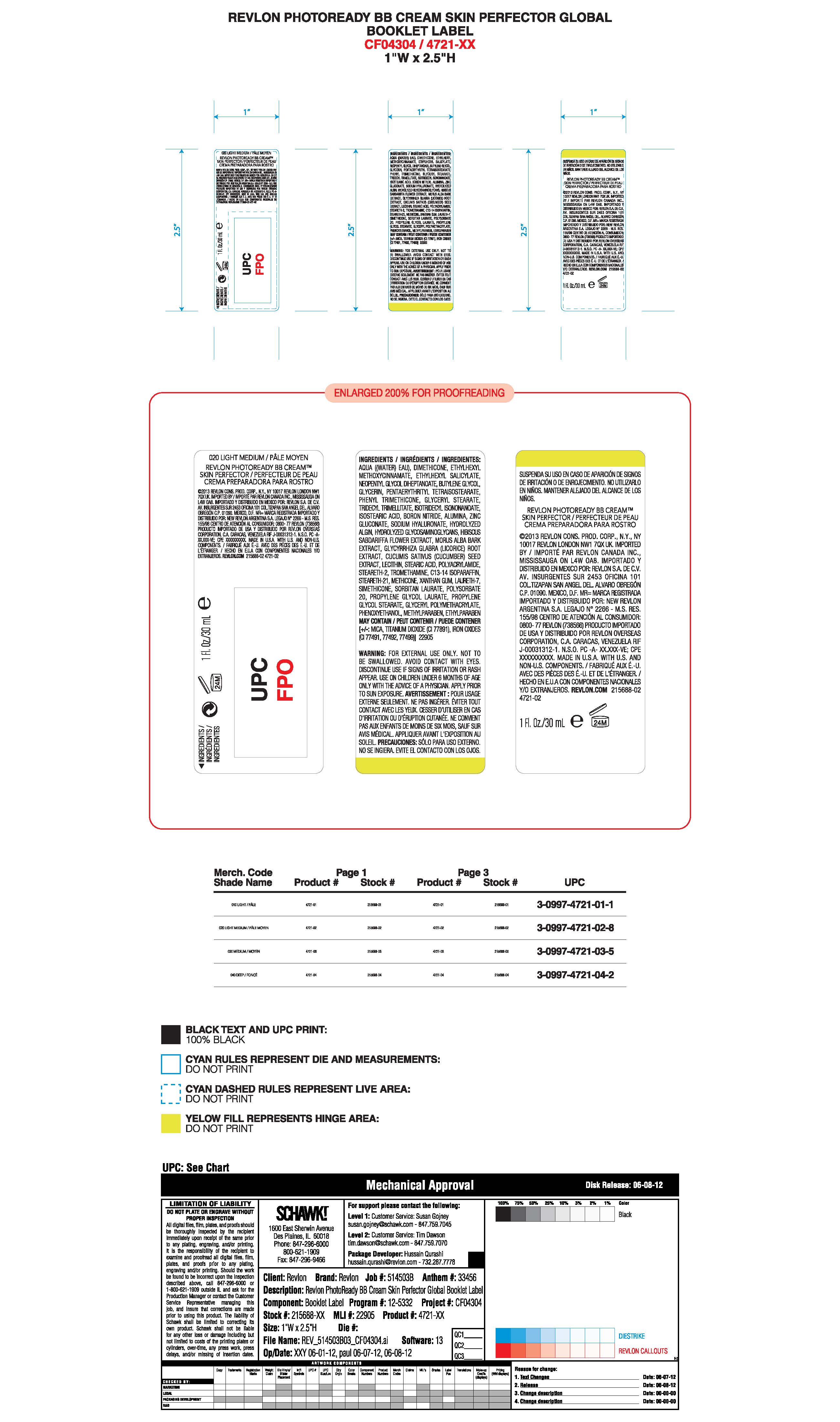 DRUG LABEL: Revlon PhotoReady BB Cream Skin Perfector
NDC: 10967-623 | Form: LIQUID
Manufacturer: Revlon Consumer Products Corp
Category: otc | Type: HUMAN OTC DRUG LABEL
Date: 20241231

ACTIVE INGREDIENTS: OCTINOXATE 7.5 mg/1 mL; OCTISALATE 5 mg/1 mL; TITANIUM DIOXIDE 6.5 mg/1 mL
INACTIVE INGREDIENTS: WATER; DIMETHICONE; NEOPENTYL GLYCOL DIHEPTANOATE; BUTYLENE GLYCOL; GLYCERIN; PENTAERYTHRITYL TETRAISOSTEARATE; PHENYL TRIMETHICONE; GLYCERYL STEARATE SE; TRIDECYL TRIMELLITATE; ISOTRIDECYL ISONONANOATE; ISOSTEARIC ACID; BORON NITRIDE; ALUMINUM HYDROXIDE; ZINC GLUCONATE; HIBISCUS SABDARIFFA FLOWER; MORUS ALBA BARK; GLYCYRRHIZA GLABRA; CUCUMIS SATIVUS LEAF; LECITHIN, SOYBEAN; STEARIC ACID; POLYACRYLAMIDE (1500 MW); STEARETH-2; TROMETHAMINE; C13-14 ISOPARAFFIN; STEARETH-21; METHICONE (20 CST); XANTHAN GUM; LAURETH-7; POLYSORBATE 20; PROPYLENE GLYCOL LAURATES; PROPYLENE GLYCOL STEARATE; PHENOXYETHANOL; METHYLPARABEN; ETHYLPARABEN

Revlon Photoready BB Cream Skin Perfector

Active Ingredients:

Octinoxate 7.5%

Octosalate 5.0%

Titanium Dioxide 6.5%

Purpose:

Sunscreen

Uses:

- Helps prevent sunburn
- If used as directed with other sun protection measures (see Directions), decreases the risk of skin cancer and early skin aging caused by the sun

Warnings:

- For external use only
- Do notuse on damaged or broken skin
- When using this product: Keep out of eyes. Rinse with water to remove.
- Stop use and ask a doctor if a rash occurs
- Keep out of reach of children. If product is swallowed, get medical help or contact a Poison Control center right away

Directions:

- Apply liberally 15 minutes before sun exposure
- Use a water resistant sunscreen if swimming or sweating
- Reapply at least every 2 hours
- Children under 6 months: Ask a doctor.

Sun Protection Measures:

Spending time in the sun increases your risk of skin cancer and early skin aging. To decrease this risk, regularly use a sunscreen with a Broad Spectrum SPF value of 15 or higher and other sun protection measures including:

- Limit time in the sun, especially from 10 am - 2 pm
- Wear long-sleeved shirts, pants, hats and sunglasses.

Inactive Ingredients:

Aqua ((Water) Eau), Dimethicone, Neopentyl Glycol Diheptanoate, Butylene Glycol, Glycerin, Pentaerythrityl Tetraisostearate, Phenyl Trimethicone, Glyceryl Stearate, Tridecyl Trimellitrate, Isotridecyl Isonononanoate, Isostearic Acid, Boron Nitride, Alumina, Zinc Gluconate, Sodium Hyaluronate, Hydrogenated Algin, Hydrolyzed Glycosaminoglycine, Hibiscus Sabdariffa Flower Extract, Morus Alba Bark Extract, Glucyrrhiza Glabra (Licorice) Root Extract, Cucumis Sativis (Cucumber) Seed Extrract, Stearic Acid, Polyacrylamide, Steareth-2, Tromethamine, C13-14 Isoparaffin, Steareth-21, Methicone, Xanthan Gum, Laureth-7, Simethicone, Sorbitan Laurate, Polysorbate 20, Propylene Glycol Laurate, Propylene Glycol Stearate, Glyceryl Polymethacrylate, Phenoxyethanol, Methylparaben, Ethylparaben May Contain: Mica, Titanium Dioxide (CI 77981), Iron Oxides (CI 77491, 77492, 77499)

DOSAGE AND ADMINISTRATION

Apply liberally 15 minutes before sun exposure.

KEEP OUT OF REACH OF CHILDREN

Keep out of the reach of children. If product is swallowed, get medical help or contact a Poison Control Center right away.

PURPOSE

Sunscreen

Principal Display Panel:

REVLON

PHOTOREADY BB CREAM

SKIN PERFECTOR

BROAD SPECTRUM

SPF 30

1.0 fL. OZ/30 mL